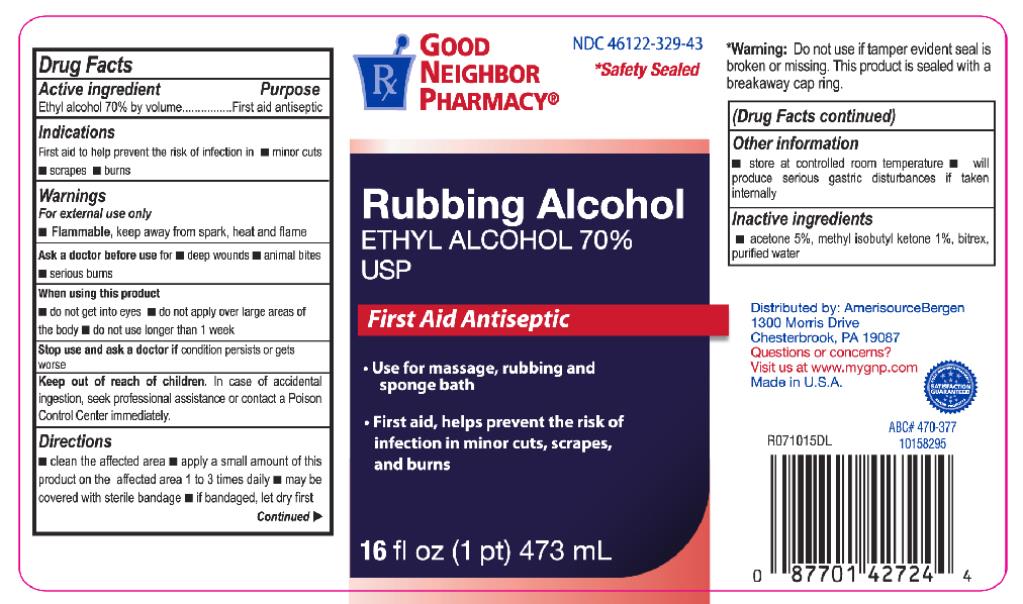 DRUG LABEL: Ethyl Rubbing Alcohol 70 Percent
NDC: 82645-926 | Form: LIQUID
Manufacturer: Pharma Nobis, LLC
Category: otc | Type: HUMAN OTC DRUG LABEL
Date: 20231226

ACTIVE INGREDIENTS: ALCOHOL 700 mg/1 mL
INACTIVE INGREDIENTS: ACETONE; METHYL ISOBUTYL KETONE; DENATONIUM BENZOATE; WATER

Private Label Ethyl Rubbing Alcohol 70 Percent USP

Drug Facts

Active Ingredient

Ethyl Alcohol 70% by volume

Purpose

First aid antiseptic

Use

First aid to help prevent the risk of infection in.

- minor cuts
- scrapes
- burns

Warnings

For external use only.

- Flammable, keep way from spark, heat and flame.

Ask a doctor before use for

- deep wounds
- animal bites
- serious burns

When using this product

- do not get into eyes
- do not apply over large areas of the body
- do not use longer than 1 week

Stop use and ask a doctor if

condition persists or gets worse

Keep out of reach of children.

In case of accidental ingestion, seek professional assistance or contact a Poison Control Center immediately.

Directions

- clean the affected area.
- apply a small amount of this product on the affected area 1 to 3 times daily.
- may be covered with sterile bandage.
- if bandaged, let it dry first.

Other Information

- store at room temperature
- will produce serious gastric disturbances if taken internally.

Inactive Ingredient

Acetone 5%

Methyl isobutyl ketone 1%

bitrex

purified water

Principal Display Panel

NDC 46122-329-43
RUBBING ALCOHOL
ETHYL ALCOHOL 70%
USP
First Aid Antiseptic
16 fl oz (1 pt) 473 mL